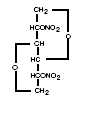 DRUG LABEL: Unknown
Manufacturer: Reddy Pharmaceuticals, LLC
Category: prescription | Type: Human prescription drug label
Date: 20070331

DESCRIPTION

Isosorbide mononitrate is 1,4:3,6-dianhydro-D-glucitol, 5-nitrate, an organic nitrate whose structural formula is:

and whose molecular weight is 191.14. The organic nitrates are vasodilators, active on both arteries and veins. Each Ismo® tablet contains 20 mg of isosorbide mononitrate. The inactive ingredients in each tablet are colloidal silicon dioxide, D&C Yellow 10 Aluminum Lake, FD&C Yellow 6 Aluminum Lake, hydroxypropyl methylcellulose, lactose, magnesium stearate, microcrystalline cellulose, polyethylene glycol, polysorbate 20, povidone, sodium starch glycolate, titanium dioxide and hydroxypropyl cellulose.

CLINICAL PHARMACOLOGY

Isosorbide mononitrate is the major active metabolite of isosorbide dinitrate (ISDN), and most of the clinical activity of the dinitrate is attributable to the mononitrate.

The principal pharmacological action of isosorbide mononitrate, due to its nitric oxide metabolite, is direct relaxation of vascular smooth muscle. The result is dilatation of peripheral arteries and veins, especially the latter. Dilation of the veins promotes peripheral pooling of blood and decreases venous return to the heart, thereby reducing left ventricular end-diastolic pressure and pulmonary capillary wedge pressure (preload). Arteriolar relaxation reduces systemic vascular resistance, systolic arterial pressure, and mean arterial pressure (afterload). Dilatation of the coronary arteries also occurs. The relative importance of preload reduction, afterload reduction, and coronary dilatation remains undefined.

Pharmacodynamics

Dosing regimens for most chronically used drugs are designed to provide plasma concentrations that are continu-ously greater than a minimally effective concentration. This strategy is inappropriate for organic nitrates. Several well-controlled clinical trials have used exercise testing to assess the antianginal efficacy of continuously delivered nitrates. In the large majority of these trials, active agents were indistinguishable from placebo after 24 hours (or less) of continuous therapy. Attempts to overcome tolerance by dose escalation, even to doses far in excess of those used acutely, have consistently failed. Only after nitrates have been absent from the body for several hours has their antianginal efficacy been restored. The drug-free interval sufficient to avoid tolerance to isosorbide mononitrate has not been completely defined. In the only regimen of twice-daily isosorbide mononitrate that has been shown to avoid development of tolerance, the two doses of Ismo tablets are given 7 hours apart, so there is a gap of 17 hours between the second dose of each day and the first dose of the next day. Taking account of the relatively long half-life of isosorbide mononitrate this result is consistent with those obtained for other organic nitrates. The same twice-daily regimen of Ismo tablets successfully avoided significant rebound/withdrawal effects. The incidence and magnitude of such phenomena have appeared, in studies of other nitrates, to be highly dependent upon the schedule of nitrate administration.

Pharmacokinetics

In humans, isosorbide mononitrate is not subject to first pass metabolism in the liver. The absolute bioavailability of isosorbide mononitrate from Ismo tablets is nearly 100%. Maximum serum concentrations of isosorbide mononitrate are achieved 30 to 60 minutes after ingestion of Ismo. The volume of distribution of isosorbide mononitrate is approximately 0.6 L/kg, and less than 4% is bound to plasma proteins. It is cleared from the serum by denitration to isosorbide; glucuronidation to the mononitrate glucuronide; and denitration/hydration to sorbitol. None of these metabolites is vasoactive. Less than 1% of administered isosorbide mononitrate is eliminated in the urine. The overall elimination half-life of isosorbide mononitrate is about 5 hours; the rate of clearance is the same in healthy young adults , in patients with various degrees of renal, hepatic, or cardiac dysfunction, and in the elderly. In a single-dose study, the pharmacokinetics of isosorbide mononitrate were dose-proportional up to at least 60 mg.

Clinical Trials

Controlled trials of single doses of Ismo tablets have demonstrated that antianginal activity is present about 1 hour after dosing, with peak effect seen from 1 to 4 hours after dosing. In placebo-controlled trials lasting 2 to 3 weeks, Ismo tablets were administered twice daily, in asymmetric regimens (with interdosing intervals of 7 and 17 hours) designed to avoid tolerance. One trial tested doses of 10 mg and 20 mg; one trial tested doses of 20 mg, 40 mg, and 60 mg; and three trials tested only doses of 20 mg. In each trial, the subjects were persons with known chronic stable angina, and the primary measure of efficacy was exercise tolerance on a standardized treadmill test. After initial dosing and for at least 3 weeks, exercise tolerance in patients treated with Ismo 20 mg tablets was significantly greater than that seen in patients treated with placebo, although there was some attenuation of effect with time. Treatment with Ismo tablets was superior to placebo for at least 12 hours after the first dose (i.e., 5 hours after the second dose) of each day. Significant tolerance and rebound phenomena were not observed. The 10-mg dose was not unequivocally superior to placebo, while the effect of the 40-mg dose was similar to that of the 20-mg dose. The 60-mg dose appeared to be less effective, and it was associated with a rebound phenomenon (early-morning worsening).

INDICATIONS AND USAGE

Ismo tablets are indicated for the prevention of angina pectoris due to coronary artery disease. The onset of action of oral isosorbide mononitrate is not sufficiently rapid for this product to be useful in aborting an acute anginal episode.

CONTRAINDICATIONS

Allergic reactions to organic nitrates are extremely rare, but they do occur. Isosorbide mononitrate is contraindicated in patients who are allergic to it.

WARNINGS

Amplification of the vasodilatory effects of Ismo by sildenafil can result in severe hypotension. The time course and dose dependence of this interaction have not been studied. Appropriate supportive care has not been studied, but it seems reasonable to treat this as a nitrate overdose, with elevation of the extremities and with central volume expansion.

The benefits of isosorbide mononitrate in patients with acute myocardial infarction or congestive heart failure have not been established. Because the effects of isosorbide mononitrate are difficult to terminate rapidly, this drug is not recommended in these settings. If isosorbide mononitrate is used in these conditions, careful clinical or hemo-dynamic monitoring must be used to avoid the hazards of hypotension and tachycardia.

PRECAUTIONS

General

Severe hypotension, particularly with upright posture, may occur with even small doses of isosorbide mononitrate. This drug should therefore be used with caution in patients who may be volume depleted or who, for whatever reason, are already hypotensive. Hypotension induced by isosorbide mononitrate may be accompanied by paradoxical bradycardia and increased angina pectoris. Nitrate therapy may aggravate the angina caused by hypertrophic cardiomyopathy. In industrial workers who have had long-term exposure to unknown (presumably high) doses of organic nitrates, tolerance clearly occurs. Chest pain, acute myocardial infarction, and even sudden death have occurred during temporary withdrawal of nitrates from these workers, demonstrating the existence of true physical dependence. The importance of these observations to the routine, clinical use of oral isosorbide mononitrate is not known.

Information for Patients

Patients should be told that the antianginal efficacy of Ismo tablets can be maintained by carefully following the prescribed schedule of dosing (two doses taken 7 hours apart). For most patients, this can be accomplished by taking the first dose on awakening and the second dose 7 hours later. As with other nitrates, daily headaches sometimes accompany treatment with isosorbide mononitrate. In patients who get these headaches, the headaches are a marker of the activity of the drug. Patients should resist the temptation to avoid headaches by altering the schedule of their treatment with isosorbide mononitrate, since loss of headache may be associated with simultaneous loss of antianginal efficacy. Aspirin and/or acetaminophen, on the other hand, often successfully relieve isosorbide mononitrate-induced headaches with no deleterious effect on isosorbide mononitrate’s antianginal efficacy. Treatment with isosorbide mononitrate may be associated with lightheadedness on standing, especially just after rising from a recumbent or seated position. This effect may be more frequent in patients who have also consumed alcohol.

Drug Interactions:

The vasodilating effects of isosorbide mononitrate may be additive with those of other vasodilators. Alcohol, in particular, has been found to exhibit additive effects of this variety. Marked symptomatic orthostatic hypotension has been reported when calcium channel blockers and organic nitrates were used in combination. Dose adjustments of either class of agents may be necessary.

Carcinogenesis, Mutagenesis, Impairment of Fertility:

No carcinogenic effects were observed in mice exposed to oral isosorbide mononitrate for 104 weeks at doses of up to 900 mg/kg/day (102 X the human exposure comparing body surface area). Rats treated with 900 mg/kg/day for 26 weeks (225 X the human exposure comparing body surface area) and 500 mg/kg/day for the remaining 95 to 111 weeks (males and females, respectively) showed no evidence of tumors. No mutagenic activity was seen in a variety of in vitro and in vivo assays. No adverse effects on fertility were observed when isosorbide mononitrate was administered to male and female rats at doses of up to 500 mg/kg/day (125 X the human exposure comparing body surface area).

Pregnancy Category C

Isosorbide mononitrate has been shown to be associated with stillbirths and neonatal death in rats receiving 500 mg/kg/day of isosorbide mononitrate (125 X the human exposure comparing body surface area). At 250 mg/kg/day, no adverse effects on reproduction and development were reported. In rats and rabbits receiving isosorbide mononitrate at up to 250 mg/kg/day, no developmental abnormalities, fetal abnormalities, or other effects upon reproductive performance were detected; these doses are larger than the maximum recommended human dose by factors between 70 (body-surface-area basis in rabbits) and 310 (body-weight basis, either species). In rats receiving 500 mg/kg/day, there were small but statistically significant increases in the rates of prolonged gestation, prolonged parturition, stillbirth, and neonatal death; and there were small but statistically significant decreases in birth weight, live litter size, and pup survival.

There are no adequate and well-controlled studies in pregnant women. Isosorbide mononitrate should be used during pregnancy only if the potential benefit justifies the potential risk to the fetus.

Nursing Mothers:

It is not known whether isosorbide mononitrate is excreted in human milk. Because many drugs are excreted in human milk, caution should be exercised when isosorbide mononitrate is administered to a nursing woman.

Pediatric Use:

Safety and effectiveness of isosorbide mononitrate in pediatric patients have not been established.

Geriatric Use

Clinical studies of Ismo® did not include sufficient numbers of subjects aged 65 and over to determine whether they respond differently from younger subjects. Other reported clinical experience has not identified differences in responses between the elderly and younger patients. In general, dose selection for an elderly patient should be cautious, usually starting at the low end of the dosing range, although age, renal, hepatic or cardiac dysfunction do not appear to have a clinically significant effect on the clearance of Ismo®.

ADVERSE REACTIONS

The table below shows the frequencies of the adverse reactions observed in more than 1% of the subjects (a) in 6 placebo-controlled domestic studies in which patients in the active-treatment arm received 20 mg of isosorbide mononitrate twice daily, and (b) in all studies in which patients received isosorbide mononitrate in a variety of regimens. In parentheses, the same table shows the frequencies with which these adverse reactions led to discontinuation of treatment. Overall, 11% of the patients who received isosorbide mononitrate in the six controlled U.S. studies discontinued treatment because of adverse reactions. Most of these discontinued because of headache. “Dizziness” and nausea were also frequently associated with withdrawal from these studies.

Frequency of Adverse Reactions (Discontinuations) [Some individuals discontinued for multiple reasons.]
 | 6 Controlled Studies |  | 92 Clinical Studies
Dose | Placebo | 20 mg | (varied)
Patients | 204 | 219 | 3344
Headache | 9% (0%) | 38% (9%) | 19% (4.3%)
Dizziness | 1% (0%) | 5% (1%) | 3% (0.2%)
Nausea, Vomiting | <1% (0%) | 4% (3%) | 2% (0.2%)

Other adverse reactions, each reported by fewer than 1% of exposed patients, and in many cases of uncertain relation to drug treatment, were::

Cardiovascular: angina pectoris, arrhythmias, atrial fibrillation, hypotension, palpitations, postural hypotension, premature ventricular contractions, supraventricular tachycardia, syncope.

Dermatologic: pruritus, rash.

Gastrointestinal: abdominal pain, diarrhea, dyspepsia, tenesmus, tooth disorder, vomiting.

Genitourinary: dysuria, impotence, urinary frequency.

Miscellaneous: asthenia, blurred vision, cold sweat, diplopia, edema, malaise, neck stiffness, rigors.

Musculoskeletal: arthralgia.

Neurological: agitation, anxiey, confusion, dyscoordination, hypoesthesia, hypokinesia, increased appetite, insomnia, nervousness, nightmares.

Respiratory: bronchitis, pneumonia, upper-respiratory tract infection.

Extremely rarely, ordinary doses of organic nitrates have caused methemoglobinemia in normal-seeming patients; for futher discussion of its diagnosis and treatment see under OVERDOSAGE.

OVERDOSAGE

Hemodynamic Effects

The ill effects of isosorbide mononitrate overdose are generally the results of isosorbide mononitrate’s capacity to induce vasodilatation, venous pooling, reduced cardiac output, and hypotension. These hemodynamic changes may have protean manifestations, including increased intracranial pressure, with any or all of persistent throbbing headache, confusion, and moderate fever; vertigo; palpitations; visual disturbances; nausea and vomiting (possibly with colic and even bloody diarrhea); syncope (especially in the upright posture); air hunger and dyspnea, later followed by reduced ventilatory effort; diaphoresis, with the skin either flushed or cold and clammy; heart block and bradycardia; paralysis; coma; seizures and death.

Laboratory determinations of serum levels of isosorbide mononitrate and its metabolites are not widely available, and such determinations have, in any event, no established role in the management of isosorbide mononitrate overdose. There are no data suggesting what dose of isosorbide mononitrate is likely to be life-threatening in humans. In rats and mice, there is significant lethality at doses of 2000 mg/kg and 3000 mg/kg, respectively. No data are available to suggest physiological maneuvers (e.g., maneuvers to change the pH of the urine) that might accelerate elimination of isosorbide mononitrate. In particular, dialysis is known to be ineffective in removing isosorbide mononitrate from the body. No specific antagonist to the vasodilator effects of isosorbide mononitrate is known, and no intervention has been subject to controlled study as a therapy of isosorbide mononitrate overdose. Because the hypotension associated with isosorbide mononitrate overdose is the result of venodilatation and arterial hypovolemia, prudent therapy in this situation should be directed toward an increase in central fluid volume. Passive elevation of the patient’s legs may be sufficient, but intravenous infusion of normal saline or similar fluid may also be necessary. The use of epinephrine or other arterial vasoconstrictors in this setting is likely to do more harm than good. In patients with renal disease or congestive heart failure, therapy resulting in central volume expansion is not without hazard. Treatment of isosorbide mononitrate overdose in these patients may be subtle and difficult, and invasive monitoring may be required.

Methemoglobinemia

Methemoglobinemia has been reported in patients receiving other organic nitrates, and it probably could also occur as a side effect of isosorbide mononitrate. Certainly nitrate ions liberated during metabolism of isosorbide mononitrate can oxidize hemoglobin into methemoglobin. Even in patients totally without cytochrome b5 reductase activity, however, and even assuming that the nitrate moiety of isosorbide mononitrate is quantitatively applied to oxidation of hemoglobin, about 2 mg/kg of isosorbide mononitrate should be required before any of these patients manifests clinically significant (≥10%) methemoglobinemia. In patients with normal reductase function, significant production of methemoglobin should require even larger doses of isosorbide mononitrate. In one study in which 36 patients received 2 to 4 weeks of continuous nitroglycerin therapy at 3.1 to 4.4 mg/hr (equivalent, in total administered dose of nitrate ions, to 7.8 to 11.1 mg of isosorbide mononitrate per hour), the average methemoglobin level measured was 0.2%; this was comparable to that observed in parallel patients who received placebo. Notwithstanding these observations, there are case reports of significant methemoglobinemia in association with moderate overdoses of organic nitrates. None of the affected patients had been thought to be unusually susceptible.

Methemoglobin levels are available from most clinical laboratories. The diagnosis should be suspected in patients who exhibit signs of impaired oxygen delivery despite adequate cardiac output and adequate arterial pO2. Classically, methemoglobinemic blood is described as chocolate brown, without color change on exposure to air. When methemoglobinemia is diagnosed, the treatment of choice is methylene blue, 1 to 2 mg/kg intravenously.

DOSAGE AND ADMINISTRATION (SEE INDICATIONS AND USAGE)

The recommended regimen of Ismo tablets is 20 mg (one tablet) twice daily, with the two doses given 7 hours apart. For most patients, this can be accomplished by taking the first dose on awakening and the second dose 7 hours later. Dosage adjustments are not necessary for elderly patients or patients with altered renal or hepatic function. As noted above (CLINICAL PHARMACOLOGY), multiple studies of organic nitrates have shown that maintenance of continuous 24-hour plasma levels results in refractory tolerance. The dosing regimen for Ismo tablets provides a daily nitrate-free interval to avoid the development of this tolerance.

As also noted under CLINICAL PHARMACOLOGY, well-controlled studies have shown that tolerance to Ismo tablets is avoided when using the twice-daily regimen in which the two doses are given 7 hours apart. This regimen has been shown to have antianginal efficacy beginning 1 hour after the first dose and lasting at least 5 hours after the second dose. The duration (if any) of antianginal activity beyond 12 hours has not been studied; large controlled studies with other nitrates suggest that no dosing regimen should be expected to provide more than about 12 hours of continuous antianginal efficacy per day.

In clinical trials, Ismo tablets have been administered in a variety of regimens. Single doses less than 20 mg have not been adequately studied, while single doses greater than 20 mg have demonstrated no greater efficacy than doses of 20 mg.

HOW SUPPLIED

Ismo® (isosorbide mononitrate) tablets, 20 mg, are available in bottles of 100 (NDC 67857-702-01). Each orange, round, film-coated tablet is engraved “ISMO 20” on one side and scored on the reverse side.

Store at 20 - 25° C (68 -77° F) [See USP Controlled Room Temperature].

Dispense in tight container.

Manufactured by:

West-ward Pharmaceutical Corp.

Eatontown, NJ 07724

Manufactured for:

Reddy Pharmaceuticals, LLC

Bridgewater, NJ 08807